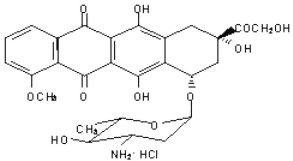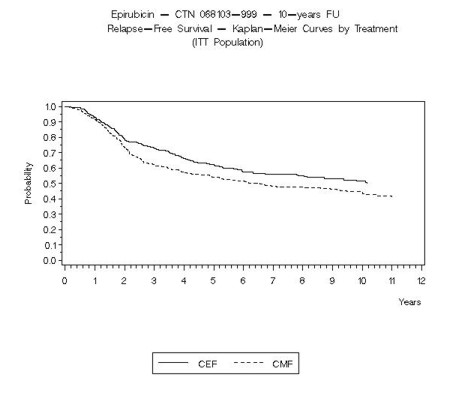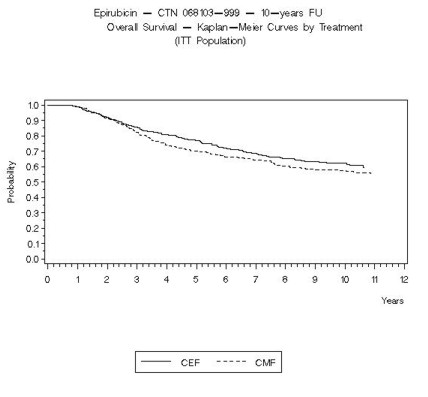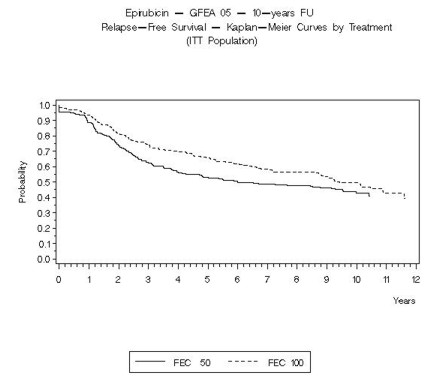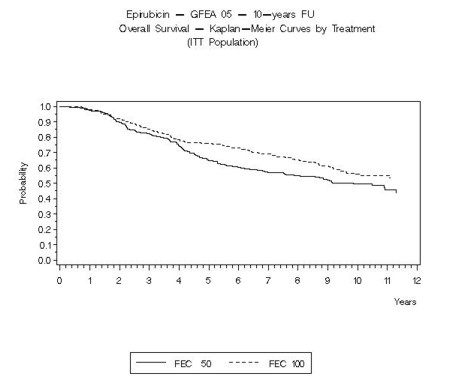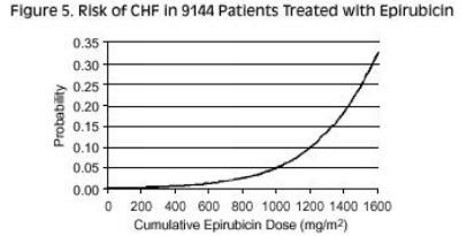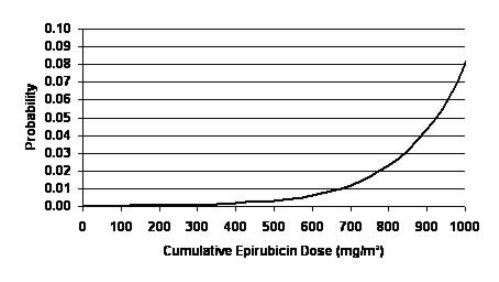 DRUG LABEL: Unknown
Manufacturer: OTN Generics Inc.
Category: prescription | Type: HUMAN PRESCRIPTION DRUG LABEL
Date: 20080611

Epirubicin Hydrochloride Injection

WARNING

1. Severe local tissue necrosis will occur if there is extravasation during administration (See PRECAUTIONS). Epirubicin must not be given by the intramuscular or subcutaneous route.
2. Myocardial toxicity, manifested in its most severe form by potentially fatal congestive heart failure (CHF), may occur either during therapy with epirubicin or months to years after termination of therapy. The probability of developing clinically evident CHF is estimated as approximately 0.9% at a cumulative dose of 550 mg/m^2, 1.6% at 700 mg/m^2, and 3.3% at 900 mg/m^2. In the adjuvant treatment of breast cancer, the maximum cumulative dose used in clinical trials was 720 mg/m^2. The risk of developing CHF increases rapidly with increasing total cumulative doses of epirubicin in excess of 900 mg/m^2; this cumulative dose should only be exceeded with extreme caution. Active or dormant cardiovascular disease, prior or concomitant radiotherapy to the mediastinal/pericardial area, previous therapy with other anthracyclines or anthracenediones, or concomitant use of other cardiotoxic drugs may increase the risk of cardiac toxicity. Cardiac toxicity with epirubicin may occur at lower cumulative doses whether or not cardiac risk factors are present.
3. Secondary acute myelogenous leukemia (AML) has been reported in patients with breast cancer treated with anthracyclines, including epirubicin. The occurrence of refractory secondary leukemia is more common when such drugs are given in combination with DNA-damaging antineoplastic agents, when patients have been heavily pretreated with cytotoxic drugs, or when doses of anthracyclines have been escalated. The cumulative risk of developing treatment-related AML or myelodysplastic syndrome (MDS), in 7110 patients with breast cancer who received adjuvant treatment with epirubicin-containing regimens, was estimated as 0.27% at 3 years, 0.46% at 5 years and 0.55% at 8 years.
4. Dosage should be reduced in patients with impaired hepatic function (see DOSAGE AND ADMINISTRATION).
5. Severe myelosuppression may occur.
6. Epirubicin should be administered only under the supervision of a physician who is experienced in the use of cancer chemotherapeutic agents.

DESCRIPTION

Epirubicin is an anthracycline cytotoxic agent, intended for intravenous administration. Epirubicin is supplied as a sterile, clear, red solution and is available in polypropylene vials containing 50 and 200 mg of epirubicin hydrochloride as a preservative-free, ready-to-use solution. Each milliliter of solution contains 2 mg of epirubicin hydrochloride. Inactive ingredients include sodium chloride, USP, and water for injection, USP. The pH of the solution has been adjusted to 3.0 with hydrochloric acid, NF.

Epirubicin hydrochloride is the 4-epimer of doxorubicin and is a semi-synthetic derivative of daunorubicin. The chemical name is (8S- cis)-10-[(3-amino-2,3,6-trideoxy-α-L- arabino-hexopyranosyl)oxy]-7,8,9,10- tetrahydro6,8,11-trihydroxy-8-(hydroxyacetyl)-1-methoxy-5,12-naphthacenedione hydrochloride. The active ingredient is a red-orange hygroscopic powder, with the empirical formula C27 H29 NO11 HCl and a molecular weight of 579.95. The structural formula is as follows:

CLINICAL PHARMACOLOGY

Epirubicin is an anthracycline cytotoxic agent. Although it is known that anthracyclines can interfere with a number of biochemical and biological functions within eukaryotic cells, the precise mechanisms of epirubicin's cytotoxic and/or antiproliferative properties have not been completely elucidated.

Epirubicin forms a complex with DNA by intercalation of its planar rings between nucleotide base pairs, with consequent inhibition of nucleic acid (DNA and RNA) and protein synthesis.

Such intercalation triggers DNA cleavage by topoisomerase II, resulting in cytocidal activity. Epirubicin also inhibits DNA helicase activity, preventing the enzymatic separation of double-stranded DNA and interfering with replication and transcription. Epirubicin is also involved in oxidation/reduction reactions by generating cytotoxic free radicals. The antiproliferative and cytotoxic activity of epirubicin is thought to result from these or other possible mechanisms.

Epirubicin is cytotoxic in vitro to a variety of established murine and human cell lines and primary cultures of human tumors. It is also active in vivo against a variety of murine tumors and human xenografts in athymic mice, including breast tumors.

Pharmacokinetics

Epirubicin pharmacokinetics are linear over the dose range of 60 to 150 mg/m^2 and plasma clearance is not affected by the duration of infusion or administration schedule. Pharmacokinetic parameters for epirubicin following 6- to 10-minute, single-dose intravenous infusions of epirubicin at doses of 60 to 150 mg/m^2 in patients with solid tumors are shown in Table 1. The plasma concentration declined in a triphasic manner with mean half-lives for the alpha, beta, and gamma phases of about 3 minutes, 2.5 hours, and 33 hours, respectively.

Table 1. Summary of Mean (±SD) Pharmacokinetic Parameters in Patients [Advanced solid tumor cancers, primarily of the lung] with Solid Tumors Receiving Intravenous Epirubicin 60 to 150 mg/m^2
Dose [N=6 patients per dose level] (mg/m^2) | Cmax [Plasma concentration at the end of 6 to 10 minute infusion] (µg/mL) | (µg∙h/mL) AUC [Area under the plasma concentration curve] | t 1/2 [Half-life of terminal phase] (hours) | CL [Plasma clearance] (L/hour) | Vss [Steady state volume of distribution] (L/kg)
60 | 5.7± 1.6 | 1.6 ± 0.2 | 35.3± 9 | 65 ± 8 | 21 ± 2
75 | 5.3± 1.5 | 1.7 ± 0.3 | 32.1± 5 | 83 ± 14 | 27 ± 11
120 | 9.0± 3.5 | 3.4 ± 0.7 | 33.7± 4 | 65 ± 13 | 23 ± 7
150 | 9.3± 2.9 | 4.2 ± 0.8 | 31.1± 6 | 69 ± 13 | 21 ± 7

Distribution

Following intravenous administration, epirubicin is rapidly and widely distributed into the tissues. Binding of epirubicin to plasma proteins, predominantly albumin, is about 77% and is not affected by drug concentration. Epirubicin also appears to concentrate in red blood cells; whole blood concentrations are approximately twice those of plasma.

Metabolism

Epirubicin is extensively and rapidly metabolized by the liver and is also metabolized by other organs and cells, including red blood cells. Four main metabolic routes have been identified:

(1) reduction of the C-13 keto-group with the formation of the 13(S)-dihydro derivative, epirubicinol; (2) conjugation of both the unchanged drug and epirubicinol with glucuronic acid; (3) loss of the amino sugar moiety through a hydrolytic process with the formation of the doxorubicin and doxorubicinol aglycones; and (4) loss of the amino sugar moiety through a redox process with the formation of the 7-deoxy-doxorubicin aglycone and 7-deoxy-doxorubicinol aglycone. Epirubicinol has in vitro cytotoxic activity one-tenth that of epirubicin. As plasma levels of epirubicinol are lower than those of the unchanged drug, they are unlikely to reach in vivo concentrations sufficient for cytotoxicity. No significant activity or toxicity has been reported for the other metabolites.

Excretion

Epirubicin and its major metabolites are eliminated through biliary excretion and, to a lesser extent, by urinary excretion. Mass-balance data from 1 patient found about 60% of the total radioactive dose in feces (34%) and urine (27%). These data are consistent with those from 3 patients with extrahepatic obstruction and percutaneous drainage, in whom approximately 35% and 20% of the administered dose were recovered as epirubicin or its major metabolites in bile and urine, respectively, in the 4 days after treatment.

Pharmacokinetics in Special Populations

Age

A population analysis of plasma data from 36 cancer patients (13 males and 23 females, 20 to 73 years) showed that age affects plasma clearance of epirubicin in female patients. The predicted plasma clearance for a female patient of 70 years of age was about 35% lower than that for a female patient of 25 years of age. An insufficient number of males > 50 years of age were included in the study to draw conclusions about age-related alterations in clearance in males. Although a lower epirubicin starting dose does not appear necessary in elderly female patients, and was not used in clinical trials, particular care should be taken in monitoring toxicity when epirubicin is administered to female patients > 70 years of age. (See PRECAUTIONS.)

Gender

In patients ≤ 50 years of age, mean clearance values in adult male and female patients were similar. The clearance of epirubicin is decreased in elderly women (see Pharmacokinetics in Special Populations - Age).

Pediatric

The pharmacokinetics of epirubicin in pediatric patients have not been evaluated.

Race

The influence of race on the pharmacokinetics of epirubicin has not been evaluated.

Hepatic Impairment

Epirubicin is eliminated by both hepatic metabolism and biliary excretion and clearance is reduced in patients with hepatic dysfunction. In a study of the effect of hepatic dysfunction, patients with solid tumors were classified into 3 groups. Patients in Group 1 (n=22) had serum AST (SGOT) levels above the upper limit of normal (median: 93 IU/L) and normal serum bilirubin levels (median: 0.5 mg/dL) and were given epirubicin doses of 12.5 to 90 mg/m^2. Patients in Group 2 had alterations in both serum AST (median: 175 IU/L) and bilirubin levels (median: 2.7 mg/dL) and were treated with an epirubicin dose of 25 mg/m^2 (n=8). Their pharmacokinetics were compared to those of patients with normal serum AST and bilirubin values, who received epirubicin doses of 12.5 to 120 mg/m^2. The median plasma clearance of epirubicin was decreased compared to patients with normal hepatic function by about 30% in patients in Group 1 and by 50% in patients in Group 2. Patients with more severe hepatic impairment have not been evaluated. (See WARNINGS and DOSAGE AND ADMINISTRATION.)

Renal Impairment

No significant alterations in the pharmacokinetics of epirubicin or its major metabolite, epirubicinol, have been observed in patients with serum creatinine < 5 mg/dL. A 50% reduction in plasma clearance was reported in four patients with serum creatinine ≥ 5 mg/dL (see WARNINGS and DOSAGE AND ADMINISTRATION). Patients on dialysis have not been studied.

Drug-Drug Interactions

Taxanes

The administration of epirubicin (90 mg/m^2) immediately prior to paclitaxel (175 mg/m^2) or docetaxel (70 to 80 mg/m^2) did not affect the pharmacokinetics of epirubicin but did result in increases in systemic exposure to epirubicin's inactive metabolites epirubicinol and 7-deoxy doxorubicin aglycone. When paclitaxel (175 mg/m^2) was administered prior to epirubicin (90 mg/m^2) an increase in the AUCs of epirubicin, epirubicinol and 7-deoxy doxorubicin aglycone was seen (see PRECAUTIONS) .

Cimetidine

Coadministration of cimetidine (400 mg twice daily for 7 days starting 5 days before chemotherapy) increased the mean AUC of epirubicin (100 mg/m^2) by 50% and decreased its plasma clearance by 30% (see PRECAUTIONS).

Drugs metabolized by cytochrome P-450 enzymes

No systematic in vitro or in vivo evaluation has been performed to examine the potential for inhibition or induction by epirubicin of oxidative cytochrome P-450 isoenzymes.

CLINICAL STUDIES

Two randomized, open-label, multicenter studies evaluated the use of epirubicin injection 100 to 120 mg/m^2 in combination with cyclophosphamide and fluorouracil for the adjuvant treatment of patients with axillary-node positive breast cancer and no evidence of distant metastatic disease (Stage II or III). Study MA-5 evaluated 120 mg/m^2 of epirubicin per course in combination with cyclophosphamide and fluorouracil (CEF-120 regimen). This study randomized premenopausal and perimenopausal women with one or more positive lymph nodes to an epirubicin-containing CEF-120 regimen or to a CMF regimen. Study GFEA-05 evaluated the use of 100 mg/m^2 of epirubicin per course in combination with fluorouracil and cyclophosphamide (FEC-100). This study randomized pre- and postmenopausal women to the FEC-100 regimen or to a lower-dose FEC-50 regimen. In the GFEA-05 study, eligible patients were either required to have ≥ 4 nodes involved with tumor or, if only 1 to 3 nodes were positive, to have negative estrogen- and progesterone-receptors and a histologic tumor grade of 2 or 3. A total of 1281 women participated in these studies. Patients with T4 tumors were not eligible for either study. Table 2 shows the treatment regimens that the patients received. The primary endpoint of the trials was relapse-free survival, ie, time to occurrence of a local, regional, or distant recurrence, or disease-related death. Patients with contralateral breast cancer, second primary malignancy or death from causes other than breast cancer were censored at the time of the last visit prior to these events.

Table 2. Treatment Regimens Used in Phase 3 Studies of Patients with Early Breast Cancer
 | Treatment Groups | Agent | Regimen
MA-5 [In women who underwent lumpectomy, breast irradiation was to be administered after completion of study chemotherapy.] N=716 | CEF-120 (total, 6 cycles) [Patients also received prophylactic antibiotic therapy with trimethoprim-sulfamethoxazole or fluoroquinolone for the duration of their chemotherapy.] N=356 | Cyclophosphamide Epirubicin Fluorouracil | 75 mg/m^2 PO, d 1–14, q 28 days 60 mg/m^2 IV, d 1 & 8, q 28 days
 | CMF (total, 6 cycles) N=360 | Cyclophosphamide Methotrexate Fluorouracil | 500 mg/m^2 IV, d 1 & 8, q 28 days 100 mg/m^2 PO, d 1–14, q 28 days 40 mg/m^2 IV, d 1 & 8, q 28 days 600 mg/m^2 IV, d 1 & 8, q 28 days
GFEA-05 [All women were to receive breast irradiation after the completion of chemotherapy.] N=565 | FEC-100 (total, 6 cycles) N=276 | Fluorouracil Epirubicin Cyclophosphamide | 500 mg/m^2 IV, d 1, q 21 days 100 mg/m^2 IV, d 1, q 21 days
 | FEC-50 (total, 6 cycles) N=289 Tamoxifen 30 mg daily × 3 years, postmenopausal women, any receptor status | Fluorouracil Epirubicin Cyclophosphamide | 500 mg/m^2 IV, d 1, q 21 days 500 mg/m^2 IV, d 1, q 21 days 50 mg/m^2 IV, d 1, q 21 days 500 mg/m^2 IV, d 1, q 21 days

In the MA-5 trial, the median age of the study population was 45 years. Approximately 60% of patients had 1 to 3 involved nodes and approximately 40% had ≥ 4 nodes involved with tumor. In the GFEA-05 study, the median age was 51 years and approximately half of the patients were postmenopausal. About 17% of the study population had 1 to 3 positive nodes and 80% of patients had ≥ 4 involved lymph nodes. Demographic and tumor characteristics were well-balanced between treatment arms in each study.

The efficacy endpoints of relapse-free survival (RFS) and overall survival (OS) were analyzed using Kaplan-Meier methods in the intent-to-treat (ITT) patient populations in each study. Results for endpoints were initially analyzed after up to 5 years of follow-up and these results are presented in the text below and in Table 3. Results after up to 10 years of follow-up are presented in Table 3. In Study MA-5, epirubicin-containing combination therapy (CEF-120) showed significantly longer RFS than CMF (5-year estimates were 62% versus 53%, stratified logrank for the overall RFS p=0.013). The estimated reduction in the risk of relapse was 24% at 5 years. The OS was also greater for the epirubicin-containing CEF-120 regimen than for the CMF regimen (5-year estimate 77% versus 70%; stratified logrank for overall survival p=0.043; non-stratified logrank p=0.13). The estimated reduction in the risk of death was 29% at 5 years.

In Study GFEA-05, patients treated with the higher-dose epirubicin regimen (FEC-100) had a significantly longer 5- year RFS (estimated 65% versus 52%, logrank for the overall RFS p=0.007) and OS (estimated 76% versus 65%, logrank for the overall survival p=0.007) than patients given the lower dose regimen (FEC-50). The estimated reduction in risk of relapse was 32% at 5 years. The estimated reduction in the risk of death was 31% at 5 years. Results of follow-up up to 10 years (median follow-up = 8.8 years and 8.3 years, respectively for Study MA-5 and Study GFEA-05) are presented in Table 3.

Although the trials were not powered for subgroup analyses, in the MA-5 study improvements in favor of CEF-120 vs. CMF were observed, in RFS and OS both in patients with 1–3 node positive and in those with ≥4 node positive tumor involvement. In the GFEA-05 study improvements in RFS and OS were observed in both pre- and postmenopausal women treated with FEC-100 compared to FEC-50.

Table 3. Efficacy Results from Phase 3 Studies of Patients with Early Breast Cancer [Based on Kaplan-Meier estimates]
 | MA-5 Study |  | GFEA-05 Study
 | CEF-120 N=356 | CMF N=360 | FEC-100 N=276 | FEC-50 N=289
RFS at 5 yrs (%) | 62 | 53 | 65 | 52
Hazard ratio [Hazard ratio: CMF:CEF-120 in MA-5, FEC-50:FEC-100 in GFEA-05] | 0.76 |  | 0.68
2-sided 95% CI | (0.60, 0.96) |  | (0.52, 0.89)
Log-rank Test stratified [Patients in MA-5 were stratified by nodal status (1–3, 4–10, and >10 positive nodes), type of initial surgery (lumpectomy versus mastectomy), and by hormone receptor status (ER or PR positive (≥10 fmol), both negative (<10 fmol), or unknown status). Patients in GFEA-05 were stratified by nodal status (1–3, 4–10, and >10 positive nodes).] | (p = 0.013) |  | (p = 0.007)
OS at 5 yrs (%) | 77 | 70 | 76 | 65
Hazard ratio | 0.71 |  | 0.69
2-sided 95% CI | (0.52, 0.98) |  | (0.51, 0.92)
Log-rank Test stratified | (p = 0.043) (unstratified p = 0.13) |  | (p = 0.007)
RFS at 10 yrs (%) | 51 | 44 | 49 | 43
Hazard ratio | 0.78 |  | 0.78
2-sided 95% CI | (0.63, 0.95) |  | (0.62, 0.99)
Log-rank Test stratified | (p = 0.017) (unstratified p = 0.023) |  | (p = 0.040) (unstratified p = 0.09)
OS at 10 yrs (%) | 61 | 57 | 56 | 50
Hazard ratio | 0.82 |  | 0.75
2-sided 95% CI | (0.65, 1.04) |  | (0.58, 0.96)
Log-rank Test stratified | (p = 0.100) (unstratified p = 0.18) |  | (p = 0.023) (unstratified p = 0.039)

The Kaplan-Meier curves for RFS and OS from Study MA-5 are shown in Figures 1 and 2 and those for Study GFEA-05 are shown in Figure 3 and 4.

Figure 1. Relapse-Free Survival in Study MA-5

Figure 2. Overall Survival in Study MA-5

Figure 3. Relapse-Free Survival in Study GFEA-05

Figure 4. Overall Survival in Study GFEA-05

See Table 3 for statistics on 5 and 10 year analyses.

INDICATIONS AND USAGE

Epirubicin Injection is indicated as a component of adjuvant therapy in patients with evidence of axillary node tumor involvement following resection of primary breast cancer.

CONTRAINDICATIONS

Patients should not be treated with epirubicin Injection if they have any of the following conditions: baseline neutrophil count < 1500 cells/mm^3; severe myocardial insufficiency, recent myocardial infarction, severe arrhythmias; previous treatment with anthracyclines up to the maximum cumulative dose; hypersensitivity to epirubicin, other anthracyclines, or anthracenediones; or severe hepatic dysfunction (see WARNINGS and DOSAGE AND ADMINISTRATION).

WARNINGS

Epirubicin injection should be administered only under the supervision of qualified physicians experienced in the use of cytotoxic therapy. Before beginning treatment with epirubicin, patients should recover from acute toxicities (such as stomatitis, neutropenia, thrombocytopenia, and generalized infections) of prior cytotoxic treatment. Also, initial treatment with epirubicin should be preceded by a careful baseline assessment of blood counts; serum levels of total bilirubin, AST, and creatinine; and cardiac function as measured by left ventricular ejection function (LVEF). Patients should be carefully monitored during treatment for possible clinical complications due to myelosuppression. Supportive care may be necessary for the treatment of severe neutropenia and severe infectious complications. Monitoring for potential cardiotoxicity is also important, especially with greater cumulative exposure to epirubicin.

Hematologic Toxicity

A dose-dependent, reversible leukopenia and/or neutropenia is the predominant manifestation of hematologic toxicity associated with epirubicin and represents the most common acute dose-limiting toxicity of this drug. In most cases, the white blood cell (WBC) nadir is reached 10 to 14 days from drug administration. Leukopenia/neutropenia is usually transient, with WBC and neutrophil counts generally returning to normal values by Day 21 after drug administration. As with other cytotoxic agents, epirubicin at the recommended dose in combination with cyclophosphamide and fluorouracil can produce severe leukopenia and neutropenia. Severe thrombocytopenia and anemia may also occur. Clinical consequences of severe myelosuppression include fever, infection, septicemia, septic shock, hemorrhage, tissue hypoxia, symptomatic anemia, or death. If myelosuppressive complications occur, appropriate supportive measures (e.g., intravenous antibiotics, colony-stimulating factors, transfusions) may be required. Myelosuppression requires careful monitoring. Total and differential WBC, red blood cell (RBC), and platelet counts should be assessed before and during each cycle of therapy with epirubicin..

Cardiac Function

Cardiotoxicity is a known risk of anthracycline treatment. Anthracycline-induced cardiac toxicity may be manifested by early (or acute) or late (delayed) events. Early cardiac toxicity of epirubicin consists mainly of sinus tachycardia and/or ECG abnormalities such as non-specific ST-T wave changes, but tachyarrhythmias, including premature ventricular contractions and ventricular tachycardia, bradycardia, as well as atrioventricular and bundle-branch block have also been reported. These effects do not usually predict subsequent development of delayed cardiotoxicity, are rarely of clinical importance, and are generally not considered an indication for the suspension of epirubicin treatment. Delayed cardiac toxicity results from a characteristic cardiomyopathy that is manifested by reduced LVEF and/or signs and symptoms of congestive heart failure (CHF) such as tachycardia, dyspnea, pulmonary edema, dependent edema, hepatomegaly, ascites, pleural effusion, gallop rhythm. Life-threatening CHF is the most severe form of anthracycline-induced cardiomyopathy. This toxicity appears to be dependent on the cumulative dose of epirubicin and represents the cumulative dose-limiting toxicity of the drug. If it occurs, delayed cardiotoxicity usually develops late in the course of therapy with epirubicin or within 2 to 3 months after completion of treatment, but later events (several months to years after treatment termination) have been reported.

In a retrospective survey, including 9144 patients, mostly with solid tumors in advanced stages, the probability of developing CHF increased with increasing cumulative doses of epirubicin (Figure 5). The estimated risk of epirubicin-treated patients developing clinically evident CHF was 0.9% at a cumulative dose of 550 mg/m^2, 1.6% at 700 mg/m^2, and 3.3% at 900 mg/m^2. The risk of developing CHF in the absence of other cardiac risk factors increased steeply after an epirubicin cumulative dose of 900 mg/m^2.

In another retrospective survey of 469 epirubicin-treated patients with metastatic or early breast cancer, the reported risk of CHF was comparable to that observed in the larger study of over 9000 patients.

Given the risk of cardiomyopathy, a cumulative dose of 900 mg/m^2 epirubicin should be exceeded only with extreme caution. Risk factors (active or dormant cardiovascular disease, prior or concomitant radiotherapy to the mediastinal/pericardial area, previous therapy with other anthracyclines or anthracenediones, concomitant use of other drugs with the ability to suppress cardiac contractility) may increase the risk of cardiac toxicity. Although not formally tested, it is probable that the toxicity of epirubicin and other anthracyclines or anthracenediones is additive. Cardiac toxicity with epirubicin may occur at lower cumulative doses whether or not cardiac risk factors are present.

Although endomyocardial biopsy is recognized as the most sensitive diagnostic tool to detect anthracycline-induced cardiomyopathy, this invasive examination is not practically performed on a routine basis. Electrocardiogram (ECG) changes such as dysrhythmias, a reduction of the QRS voltage, or a prolongation beyond normal limits of the systolic time interval may be indicative of anthracycline-induced cardiomyopathy, but ECG is not a sensitive or specific method for following anthracycline-related cardiotoxicity. The risk of serious cardiac impairment may be decreased through regular monitoring of LVEF during the course of treatment with prompt discontinuation of epirubicin at the first sign of impaired function. The preferred method for repeated assessment of cardiac function is evaluation of LVEF measured by multi-gated radionuclide angiography (MUGA) or echocardiography (ECHO). A baseline cardiac evaluation with an ECG and a MUGA scan or an ECHO is recommended, especially in patients with risk factors for increased cardiac toxicity. Repeated MUGA or ECHO determinations of LVEF should be performed, particularly with higher, cumulative anthracycline doses. The technique used for assessment should be consistent through follow-up. In patients with risk factors, particularly prior anthracycline or anthracenedione use, the monitoring of cardiac function must be particularly strict and the risk-benefit of continuing treatment with epirubicin in patients with impaired cardiac function must be carefully evaluated.

Secondary Leukemia

The occurrence of secondary acute myelogenous leukemia, with or without a preleukemic phase, has been reported in patients treated with anthracyclines. Secondary leukemia is more common when such drugs are given in combination with DNA-damaging antineoplastic agents, when patients have been heavily pretreated with cytotoxic drugs, or when doses of the anthracyclines have been escalated. These leukemias can have a short 1- to 3- year latency period. An analysis of 7110 patients who received adjuvant treatment with epirubicin in controlled clinical trials as a component of poly-chemotherapy regimens for early breast cancer, showed a cumulative risk of secondary acute myelogenous leukemia or myelodysplastic syndrome (AML/MDS) of about 0.27% (approximate 95% CI, 0.14–0.40) at 3 years, 0.46% (approximate 95% CI, 0.28–0.65) at 5 years and 0.55% (approximate 95% CI, 0.33–0.78) at 8 years. The risk of developing AML/MDS increased with increasing epirubicin cumulative doses as shown in Figure 6.

The occurrence of secondary acute myelogenous leukemia, with or without a preleukemic phase, has been reported in patients treated with anthracyclines. Secondary leukemia is more common when such drugs are given in combination with DNA-damaging antineoplastic agents, when patients have been heavily pretreated with cytotoxic drugs, or when doses of the anthracyclines have been escalated. These leukemias can have a short 1- to 3- year latency period. An analysis of 7110 patients who received adjuvant treatment with epirubicin in controlled clinical trials as a component of poly-chemotherapy regimens for early breast cancer, showed a cumulative risk of secondary acute myelogenous leukemia or myelodysplastic syndrome (AML/MDS) of about 0.27% (approximate 95% CI, 0.14–0.40) at 3 years, 0.46% (approximate 95% CI, 0.28–0.65) at 5 years and 0.55% (approximate 95% CI, 0.33–0.78) at 8 years. The risk of developing AML/MDS increased with increasing epirubicin cumulative doses as shown in Figure 6.

Figure 6. Risk of AML/MDS in 7110 Patients Treated with Epirubicin

The cumulative probability of developing AML/MDS was found to be particularly increased in patients who received more than the maximum recommended cumulative dose of epirubicin (720 mg/m^2) or cyclophosphamide (6,300 mg/m^2), as shown in Table 4.

Table 4. Cumulative probability of AML/MDS in relation to cumulative doses of epirubicin and cyclophosphamide
Years from Treatment Start | Cumulative Probability of Developing AML/MDS % (95% CI)
Years from Treatment Start | Cyclophosphamide Cumulative Dose ≤6,300 mg/m^2 |  | Cyclophosphamide Cumulative Dose >6,300 mg/m^2
Years from Treatment Start | Epirubicin Cumulative Dose ≤720 mg/m^2 N=4760 | Epirubicin Cumulative Dose >720 mg/m^2 N=111 | Epirubicin Cumulative Dose ≤720 mg/m^2 N=890 | Epirubicin Cumulative Dose >720 mg/m^2 N=261
3 | 0.12 (0.01–0.22) | 0.00 (0.00–0.00) | 0.12 (0.00–0.37) | 4.37 (1.69–7.05)
5 | 0.25 (0.08–0.42) | 2. 38 (0.00–6.99) | 0.31 (0.00–0.75) | 4.97 (2.06–7.87)
8 | 0.37 (0.13–0.61) | 2. 38 (0.00–6.99) | 0.31 (0.00–0.75) | 4.97 (2.06–7.87)

Epirubicin is mutagenic, clastogenic, and carcinogenic in animals (see next section, Carcinogenesis, Mutagenesis and Impairment of Fertility).

Carcinogenesis, Mutagenesis & Impairment of Fertility

Treatment-related acute myelogenous leukemia has been reported in women treated with epirubicin-based adjuvant chemotherapy regimens (see above section, WARNINGS, Secondary Leukemia). Conventional long-term animal studies to evaluate the carcinogenic potential of epirubicin have not been conducted, but intravenous administration of a single 3.6 mg/kg epirubicin dose to female rats (about 0.2 times the maximum recommended human dose on a body surface area basis) approximately doubled the incidence of mammary tumors (primarily fibroadenomas) observed at 1 year. Administration of 0.5 mg/kg epirubicin intravenously to rats (about 0.025 times the maximum recommended human dose on a body surface area basis) every 3 weeks for ten doses increased the incidence of subcutaneous fibromas in males over an 18-month observation period. In addition, subcutaneous administration of 0.75 or 1.0 mg/kg/day (about 0.015 times the maximum recommended human dose on a body surface area basis) to newborn rats for 4 days on both the first and tenth day after birth for a total of eight doses increased the incidence of animals with tumors compared to controls during a 24-month observation period.

Epirubicin was mutagenic in vitro to bacteria (Ames test) either in the presence or absence of metabolic activation and to mammalian cells (HGPRT assay in V79 Chinese hamster lung fibroblasts) in the absence but not in the presence of metabolic activation. Epirubicin was clastogenic in vitro (chromosome aberrations in human lymphocytes) both in the presence and absence of metabolic activation and was also clastogenic in vivo (chromosome aberration in mouse bone marrow).

In fertility studies in rats, males were given epirubicin daily for 9 weeks and mated with females that were given epirubicin daily for 2 weeks prior to mating and through Day 7 of gestation. When 0.3 mg/kg/day (about 0.015 times the maximum recommended human single dose on a body surface area basis) was administered to both sexes, no pregnancies resulted. No effects on mating behavior or fertility were observed at 0.1 mg/kg/day, but male rats had atrophy of the testes and epididymis, and reduced spermatogenesis. The 0.1 mg/kg/day dose also caused embryolethality. An increased incidence of fetal growth retardation was observed in these studies at 0.03 mg/kg/day (about 0.0015 times the maximum recommended human single dose on a body surface area basis). Multiple daily doses of epirubicin to rabbits and dogs also caused atrophy of male reproductive organs. Single 20.5 and 12 mg/kg doses of intravenous epirubicin caused testicular atrophy in mice and rats, respectively (both approximately 0.5 times the maximum recommended human dose on a body surface area basis). A single dose of 16.7 mg/kg epirubicin caused uterine atrophy in rats.

Although experimental data are not available, epirubicin could induce chromosomal damage in human spermatozoa due to its genotoxic potential. Men undergoing treatment with epirubicin should use effective contraceptive methods. Epirubicin may cause irreversible amenorrhea (premature menopause) in premenopausal women.

Liver Function

The major route of elimination of epirubicin is the hepatobiliary system (see CLINICAL PHARMACOLOGY, Pharmacokinetics in Special Populations). Serum total bilirubin and AST levels should be evaluated before and during treatment with epirubicin. Patients with elevated bilirubin or AST may experience slower clearance of drug with an increase in overall toxicity. Lower doses are recommended in these patients (see DOSAGE AND ADMINISTRATION). Patients with severe hepatic impairment have not been evaluated; therefore, epirubicin should not be used in this patient population.

Renal Function

Serum creatinine should be assessed before and during therapy. Dosage adjustment is necessary in patients with serum creatinine >5 mg/dL (see DOSAGE AND ADMINISTRATION). Patients undergoing dialysis have not been studied.

Tumor-Lysis Syndrome

As with other cytotoxic agents, epirubicin may induce hyperuricemia as a consequence of the extensive purine catabolism that accompanies drug-induced rapid lysis of highly chemosensitive neoplastic cells (tumor lysis syndrome). Other metabolic abnormalities may also occur. While not generally a problem in patients with breast cancer, physicians should consider the potential for tumor-lysis syndrome in potentially susceptible patients and should consider monitoring serum uric acid, potassium, calcium, phosphate, and creatinine immediately after initial chemotherapy administration. Hydration, urine alkalinization, and prophylaxis with allopurinol to prevent hyperuricemia may minimize potential complications of tumor-lysis syndrome.

Pregnancy - Category D

Epirubicin may cause fetal harm when administered to a pregnant woman. Administration of 0.8 mg/kg/day intravenously of epirubicin to rats (about 0.04 times the maximum recommended single human dose on a body surface area basis) during Days 5 to 15 of gestation was embryotoxic (increased resorptions and post-implantation loss) and caused fetal growth retardation (decreased body weight), but was not teratogenic up to this dose. Administration of 2 mg/kg/day intravenously of epirubicin to rats (about 0.1 times the maximum recommended single human dose on a body surface area basis) on Days 9 and 10 of gestation was embryotoxic (increased late resorptions, post-implantation losses, and dead fetuses; and decreased live fetuses), retarded fetal growth (decreased body weight), and caused decreased placental weight. This dose was also teratogenic, causing numerous external (anal atresia, misshapen tail, abnormal genital tubercle), visceral (primarily gastrointestinal, urinary, and cardiovascular systems), and skeletal (deformed long bones and girdles, rib abnormalities, irregular spinal ossification) malformations. Administration of intravenous epirubicin to rabbits at doses up to 0.2 mg/kg/day (about 0.02 times the maximum recommended single human dose on a body surface area basis) during Days 6 to 18 of gestation was not embryotoxic or teratogenic, but a maternally toxic dose of 0.32 mg/kg/day increased abortions and delayed ossification. Administration of a maternally toxic intravenous dose of 1 mg/kg/day epirubicin to rabbits (about 0.1 times the maximum recommended single human dose on a body surface area basis) on Days 10 to 12 of gestation induced abortion, but no other signs of embryofetal toxicity or teratogenicity were observed. When doses up to 0.5 mg/kg/day epirubicin were administered to rat dams from Day 17 of gestation to Day 21 after delivery (about 0.025 times the maximum recommended single human dose on a body surface area basis), no permanent changes were observed in the development, functional activity, behavior, or reproductive performance of the offspring.

There are no adequate and well-controlled studies in pregnant women. Two pregnancies have been reported in women taking epirubicin. A 34-year-old woman, 28 weeks pregnant at her diagnosis of breast cancer, was treated with cyclophosphamide and epirubicin every 3 weeks for 3 cycles. She received the last dose at 34 weeks of pregnancy and delivered a healthy baby at 35 weeks. A second 34-year-old woman with breast cancer metastatic to the liver was randomized to FEC-50 but was removed from study because of pregnancy. She experienced a spontaneous abortion. If epirubicin is used during pregnancy, or if the patient becomes pregnant while taking this drug, the patient should be apprised of the potential hazard to the fetus. Women of childbearing potential should be advised to avoid becoming pregnant.

PRECAUTIONS

General

Epirubicin Injection is administered by intravenous infusion. Venous sclerosis may result from an injection into a small vessel or from repeated injections into the same vein. Extravasation of epirubicin during the infusion may cause local pain, severe tissue lesions (vesication, severe cellulitis) and necrosis. It is recommended that epirubicin be slowly administered into the tubing of a freely running intravenous infusion. Patients receiving initial therapy at the recommended starting doses of 100–120 mg/m^2 should generally have epirubicin infused over 15–20 minutes. For patients who require lower epirubicin starting doses due to organ dysfunction or who require modification of epirubicin doses during therapy, the epirubicin infusion time may be proportionally decreased, but should not be less than 3 minutes. (see DOSAGE AND ADMINISTRATION, Preparation of Infusion Solution). If possible, veins over joints or in extremities with compromised venous or lymphatic drainage should be avoided. A burning or stinging sensation may be indicative of perivenous infiltration, and the infusion should be immediately terminated and restarted in another vein. Perivenous infiltration may occur without causing pain.

Facial flushing, as well as local erythematous streaking along the vein, may be indicative of excessively rapid administration. It may precede local phlebitis or thrombophlebitis.

Patients administered the 120-mg/m^2 regimen of epirubicin as a component of combination chemotherapy should also receive prophylactic antibiotic therapy with trimethoprim-sulfamethoxazole (e.g., Septra®, Bactrim®) or a fluoroquinolone (see CLINICAL STUDIES, Early Breast Cancer, and DOSAGE AND ADMINISTRATION).

Epirubicin is emetigenic. Antiemetics may reduce nausea and vomiting; prophylactic use of antiemetics should be considered before administration of epirubicin , particularly when given in conjunction with other emetigenic drugs.

As with other anthracyclines, administration of epirubicin after previous radiation therapy may induce an inflammatory recall reaction at the site of the irradiation.

As with other cytotoxic agents, thrombophlebitis and thromboembolic phenomena, including pulmonary embolism (in some cases fatal) have been coincidentally reported with the use of epirubicin.

Information for Patients

Patients should be informed of the expected adverse effects of epirubicin, including gastrointestinal symptoms (nausea, vomiting, diarrhea, and stomatitis) and potential neutropenic complications. Patients should consult their physician if vomiting, dehydration, fever, evidence of infection, symptoms of CHF, or injection-site pain occurs following therapy with epirubicin. Patients should be informed that they will almost certainly develop alopecia. Patients should be advised that their urine may appear red for 1 to 2 days after administration of epirubicin and that they should not be alarmed. Patients should understand that there is a risk of irreversible myocardial damage associated with treatment with epirubicin, as well as a risk of treatment-related leukemia. Because epirubicin may induce chromosomal damage in sperm, men undergoing treatment with epirubicin should use effective contraceptive methods. Women treated with epirubicin may develop irreversible amenorrhea, or premature menopause.

Laboratory Testing

See WARNINGS. Blood counts, including absolute neutrophil counts, and liver function should be assessed before and during each cycle of therapy with epirubicin. Repeated evaluations of LVEF should be performed during therapy.

Drug Interactions

Epirubicin when used in combination with other cytotoxic drugs may show on-treatment additive toxicity, especially hematologic and gastrointestinal effects.

Concomitant use of epirubicin with other cardioactive compounds that could cause heart failure (e.g., calcium channel blockers), requires close monitoring of cardiac function throughout treatment.

There are few data regarding the coadministration of radiation therapy and epirubicin. In adjuvant trials of epirubicin-containing CEF-120 or FEC-100 chemotherapies, breast irradiation was delayed until after chemotherapy was completed. This practice resulted in no apparent increase in local breast cancer recurrence relative to published accounts in the literature. A small number of patients received epirubicin-based chemotherapy concomitantly with radiation therapy but had chemotherapy interrupted in order to avoid potential overlapping toxicities. It is likely that use of epirubicin with radiotherapy may sensitize tissues to the cytotoxic actions of irradiation. Administration of epirubicin after previous radiation therapy may induce an inflammatory recall reaction at the site of the irradiation.

Epirubicin is extensively metabolized by the liver. Changes in hepatic function induced by concomitant therapies may affect epirubicin metabolism, pharmacokinetics, therapeutic efficacy, and/or toxicity.

The administration of epirubicin immediately prior to paclitaxel or docetaxel does not affect the pharmacokinetics of epirubicin but does result in increases in the systemic exposure to epirubicin's inactive metabolites epirubicinol and 7-deoxy doxorubicin aglycone (see CLINICAL PHARMACOLOGY). Administration of paclitaxel prior to epirubicin resulted in an increase in epirubicin AUC compared to when epirubicin was administered prior to paclitaxel.

Cimetidine increased the AUC of epirubicin by 50%. Cimetidine treatment should be stopped during treatment with epirubicin (see CLINICAL PHARMACOLOGY).

Drug-Laboratory Test Interactions

There are no known interactions between epirubicin and laboratory tests.

Carcinogenesis, Mutagenesis & Impairment of Fertility

See WARNINGS.

Pregnancy

Pregnancy Category D

see WARNINGS.

Nursing Mothers

Epirubicin was excreted into the milk of rats treated with 0.50 mg/kg/day of epirubicin during peri- and postnatal periods. It is not known whether epirubicin is excreted in human milk. Because many drugs, including other anthracyclines, are excreted in human milk and because of the potential for serious adverse reactions in nursing infants from epirubicin, mothers should discontinue nursing prior to taking this drug.

Geriatric Use

Although a lower starting dose of epirubicin was not used in trials in elderly female patients, particular care should be taken in monitoring toxicity when epirubicin is administered to female patients ≥ 70 years of age. (See CLINICAL PHARMACOLOGY, Pharmacokinetics in Special Populations.)

Pediatric Use

The safety and effectiveness of epirubicin in pediatric patients have not been established in adequate and well-controlled clinical trials. Pediatric patients may be at greater risk for anthracycline-induced acute manifestations of cardiotoxicity and for chronic CHF.

ADVERSE REACTIONS

On-Study Events

Integrated safety data are available from two studies (Studies MA-5 and GFEA-05, see CLINICAL STUDIES) evaluating epirubicin-containing combination regimens in patients with early breast cancer. Of the 1260 patients treated in these studies, 620 patients received the higher-dose epirubicin regimen (FEC-100/CEF-120), 280 patients received the lower dose epirubicin regimen (FEC-50), and 360 patients received CMF. Serotonin-specific antiemetic therapy and colony-stimulating factors were not used in these trials. Clinically relevant acute adverse events are summarized in Table 5.

Table 5. Clinically Relevant Acute Adverse Events in Patients with Early Breast Cancer
Event | % of Patients
Event | FEC-100/CEF-120 (N=620) |  | FEC-50 (N=280) |  | CMF (N=360)
Event | Grades 1–4 | Grades ¾ | Grades 1–4 | Grades 3/4 | Grades 1–4 | Grades 3/4
Event | Hematologic Leukopenia Neutropenia Anemia Thrombocytopenia | 80.3 80.3 72.2 48.8 | 58.6 67.2 5.8 5.4 | 49.6 53.9 12.9 4.6 | 1.5 10.5 0 0 | 98.1 95.8 70.9 51.4 | 60.3 78.1 0.9 3.6
Endocrine Amenorrhea Hot flashes | 71.8 38.9 | 0 4.0 | 69.3 5.4 | 0 0 | 67.7 69.1 | 0 6.4
Body as a Whole Lethargy Fever | 45.8 5.2 | 1.9 0 | 1.1 1.4 | 0 0 | 72.7 4.5 | 0.3 0
Gastrointestinal Nausea/vomiting Mucositis Diarrhea Anorexia | 92.4 58.5 24.8 2.9 | 25.0 8.9 0.8 0 | 83.2 9.3 7.1 1.8 | 22.1 0 0 0 | 85.0 52.9 50.7 5.8 | 6.4 1.9 2.8 0.3
Infection Infection Febrile neutropenia | 21.5 NA | 1.6 6.1 | 15.0 0 | 0 0 | 25.9 NA | 0.6 1.1
Ocular Conjunctivitis/keratitis | 14.8 | 0 | 1.1 | 0 | 38.4 | 0
Skin Alopecia Local toxicity Rash/itch Skin changes | 95.5 19.5 8.9 4.7 | 56.6 0.3 0.3 0 | 69.6 2.5 1.4 0.7 | 19.3 0.4 0 0 | 84.4 8.1 14.2 7.2 | 6.7 0 0 0
FEC & CEF = cyclophosphamide + epirubicin + fluorouracil; CMF = cyclophosphamide + methotrexate + fluorouracil NA = not available
Grade 1 or 2 changes in transaminase levels were observed but were more frequently seen with CMF than with CEF.

Delayed Events

Table 6 describes the incidence of delayed adverse events in patients participating in the MA-5 and GFEA-05 trials.

Table 6. Long-Term Adverse Events in Patients with Early Breast Cancer
Event | % of Patients
Event | FEC-100/CEF-120 (N=620) | FEC-50 (N=280) | CMF (N=360)
Cardiac events Asymptomatic drops in LVEF CHF | 2.1 [In study MA-5 cardiac function was not monitored after 5 years.] 1.5 | 1.40.4 | 0.8 0.3
Leukemia AML | 0.8 | 0 | 0.3

Two cases of acute lymphoid leukemia (ALL) were also observed in patients receiving epirubicin. However, an association between anthracyclines such as epirubicin and ALL has not been clearly established.

Overview of Acute and Delayed Toxicities

Hematologic

See WARNINGS.

Gastrointestinal

A dose-dependent mucositis (mainly oral stomatitis, less often esophagitis) may occur in patients treated with epirubicin. Clinical manifestations of mucositis may include a pain or burning sensation, erythema, erosions, ulcerations, bleeding, or infections. Mucositis generally appears early after drug administration and, if severe, may progress over a few days to mucosal ulcerations; most patients recover from this adverse event by the third week of therapy. Hyperpigmentation of the oral mucosa may also occur.

Nausea, vomiting, and occasionally diarrhea and abdominal pain can also occur. Severe vomiting and diarrhea may produce dehydration. Antiemetics may reduce nausea and vomiting; prophylactic use of antiemetics should be considered before therapy (see PRECAUTIONS).

Cutaneous and Hypersensitivity Reactions

Alopecia occurs frequently, but is usually reversible, with hair regrowth occurring within 2 to 3 months from the termination of therapy. Flushes, skin and nail hyperpigmentation, photosensitivity, and hypersensitivity to irradiated skin (radiation-recall reaction) have been observed. Urticaria and anaphylaxis have been reported in patients treated with epirubicin; signs and symptoms of these reactions may vary from skin rash and pruritus to fever, chills, and shock.

Cardiovascular

See WARNINGS.

Secondary Leukemia

See WARNINGS.

Injection-Site Reactions

See PRECAUTIONS.

OVERDOSAGE

A 36-year-old man with non-Hodgkin's lymphoma received a daily 95 mg/m^2 dose of Epirubicin Injection for 5 consecutive days. Five days later, he developed bone marrow aplasia, grade 4 mucositis, and gastrointestinal bleeding. No signs of acute cardiac toxicity were observed. He was treated with antibiotics, colony-stimulating factors, and antifungal agents, and recovered completely. A 63-year-old woman with breast cancer and liver metastasis received a single 320 mg/m^2 dose of epirubicin. She was hospitalized with hyperthermia and developed multiple organ failure (respiratory and renal), with lactic acidosis, increased lactate dehydrogenase, and anuria. Death occurred within 24 hours after administration of epirubicin. Additional instances of administration of doses higher than recommended have been reported at doses ranging from 150 to 250 mg/m^2. The observed adverse events in these patients were qualitatively similar to known toxicities of epirubicin. Most of the patients recovered with appropriate supportive care.

If an overdose occurs, supportive treatment (including antibiotic therapy, blood and platelet transfusions, colony-stimulating factors, and intensive care as needed) should be provided until the recovery of toxicities. Delayed CHF has been observed months after anthracycline administration. Patients must be observed carefully over time for signs of CHF and provided with appropriate supportive therapy.

DOSAGE AND ADMINISTRATION

Epirubicin Injection is administered to patients by intravenous infusion. Epirubicin is given in repeated 3- to 4-week cycles. The total dose of Epirubicin Hydrochloride Injection may be given on Day 1 of each cycle or divided equally and given on Days 1 and 8 of each cycle. The recommended dosages of epirubicin are as follows:

Starting Doses

The recommended starting dose of epirubicin is 100 to 120 mg/m^2. The following regimens were used in the trials supporting use of epirubicin as a component of adjuvant therapy in patients with axillary-node positive breast cancer:

CEF-120: | Cyclophosphamide epirubicin 5-Fluorouracil Repeated every 28 days for 6 cycles | 75 mg/m^2 PO D 1–14 60 mg/m^2 IV D 1, 8 500 mg/m^2 IV D 1, 8
FEC-100: | 5-Fluorouracil epirubicin Cyclophosphamide | 500 mg/m^2 100 mg/m^2 500 mg/m^2
 | All drugs administered intravenously on Day 1 and repeated every 21 days for 6 cycles

Patients administered the 120-mg/m^2 regimen of epirubicin also received prophylactic antibiotic therapy with trimethoprim-sulfamethoxazole (e.g., Septra®, Bactrim®) or a fluoroquinolone.

Bone Marrow Dysfunction

Consideration should be given to administration of lower starting doses (75–90 mg/m^2) for heavily pretreated patients, patients with pre-existing bone marrow depression, or in the presence of neoplastic bone marrow infiltration (see WARNINGS and PRECAUTIONS).

Hepatic Dysfunction

Definitive recommendations regarding use of epirubicin in patients with hepatic dysfunction are not available because patients with hepatic abnormalities were excluded from participation in adjuvant trials of FEC-100/CEF-120 therapy. In patients with elevated serum AST or serum total bilirubin concentrations, the following dose reductions were recommended in clinical trials, although few patients experienced hepatic impairment:

- Bilirubin 1.2 to 3 mg/dL or AST 2 to 4 times upper limit of normal 1/2 of recommended starting dose
- Bilirubin > 3 mg/dL or AST > 4 times upper limit of normal 1/4 of recommended starting dose

Information regarding experience in patients with hepatic dysfunction is provided in CLINICAL PHARMACOLOGY, Pharmacokinetics In Special Populations.

Renal Dysfunction

While no specific dose recommendation can be made based on the limited available data in patients with renal impairment, lower doses should be considered in patients with severe renal impairment (serum creatinine > 5 mg/dL).

Dose Modifications

Dosage adjustments after the first treatment cycle should be made based on hematologic and nonhematologic toxicities. Patients experiencing during treatment cycle nadir platelet counts <50,000/mm^3, absolute neutrophil counts (ANC) <250/mm^3, neutropenic fever, or Grades 3/4 nonhematologic toxicity should have the Day 1 dose in subsequent cycles reduced to 75% of the Day 1 dose given in the current cycle. Day 1 chemotherapy in subsequent courses of treatment should be delayed until platelet counts are ≥100,000/mm^3, ANC ≥1500/mm^3, and nonhematologic toxicities have recovered to ≤ Grade 1.

For patients receiving a divided dose of epirubicin (Day 1 and Day 8), the Day 8 dose should be 75% of Day 1 if platelet counts are 75,000–100,000/mm^3 and ANC is 1000 to 1499/mm^3. If Day 8 platelet counts are <75,000/mm^3, ANC <1000/mm^3, or Grade 3/4 nonhematologic toxicity has occurred, the Day 8 dose should be omitted.

Preparation & Administration Precautions

Parenteral drug products should be inspected visually for particulate matter and discoloration prior to administration, whenever solution and container permit. Procedures normally used for proper handling and disposal of anticancer drugs should be considered for use with epirubicin. Several guidelines on this subject have been published.^1–8

Protective measures

The following protective measures should be taken when handling epirubicin:

- Personnel should be trained in appropriate techniques for reconstitution and handling.
- Pregnant staff should be excluded from working with this drug.
- Personnel handling epirubicin should wear protective clothing: goggles, gowns and disposable gloves and masks.
- A designated area should be defined for syringe preparation (preferably under a laminar flow system), with the work surface protected by disposable, plastic-backed, absorbent paper.
- All items used for reconstitution, administration or cleaning (including gloves) should be placed in high-risk, waste-disposal bags for high temperature incineration.
- Spillage or leakage should be treated with dilute sodium hypochlorite (1% available chlorine) solution, preferably by soaking, and then water. All contaminated and cleaning materials should be placed in high-risk, waste-disposal bags for incineration. Accidental contact with the skin or eyes should be treated immediately by copious lavage with water, or soap and water, or sodium bicarbonate solution. However, do not abrade the skin by using a scrub brush. Medical attention should be sought. Always wash hands after removing gloves.

Incompatibilities

Prolonged contact with any solution of an alkaline pH should be avoided as it will result in hydrolysis of the drug. epirubicin should not be mixed with heparin or fluorouracil due to chemical incompatibility that may lead to precipitation.

Epirubicin can be used in combination with other antitumor agents, but it is not recommended that it be mixed with other drugs in the same syringe.

Preparation of Infusion Solution

Epirubicin is provided as a preservative-free, ready-to-use solution.

Epirubicin should be administered into the tubing of a freely flowing intravenous infusion (0.9% sodium chloride or 5% glucose solution). Patients receiving initial therapy at the recommended starting doses of 100–120 mg/m^2 should generally have epirubicin infused over 15–20 minutes. For patients who require lower epirubicin starting doses due to organ dysfunction or who require modification of epirubicin doses during therapy, the epirubicin infusion time may be proportionally decreased, but should not be less than 3 minutes. This technique is intended to minimize the risk of thrombosis or perivenous extravasation, which could lead to severe cellulitis, vesication, or tissue necrosis. A direct push injection is not recommended due to the risk of extravasation, which may occur even in the presence of adequate blood return upon needle aspiration. Venous sclerosis may result from injection into small vessels or repeated injections into the same vein (see PRECAUTIONS). Epirubicin should be used within 24 hours of first penetration of the rubber stopper. Discard any unused solution.

HOW SUPPLIED

Epirubicin injection is available in polypropylene single-use CYTOSAFE™ vials containing 2 mg epirubicin hydrochloride per mL as a sterile, preservative-free, ready-to-use solution in the following strengths:

50 mg/25 mL single-use vial NDC 15210-404-28

200 mg/100 mL single-use vial NDC 15210-404-29

STORAGE AND HANDLING

Store refrigerated between 2°C and 8°C (36°F and 46°F). Do not freeze. Protect from light. Discard unused portion.

Storage of the solution for injection at refrigerated conditions can result in the formation of a gelled product. This gelled product will return to a slightly viscous to mobile solution after 2 to a maximum of 4 hours equilibration at controlled room temperature (15–25°C).

Rx only

Manufactured by:
Pfizer (Perth) Pty Limited, Bentley WA 6102 Australia

Manufactured for:
OTN Generics Inc.
South San Francisco, CA 94080

LAB-0351-3.0
April 2008

REFERENCES

1. ONS Clinical Practice Committee. Cancer Chemotherapy Guidelines and Recommendations for Practice. Pittsburgh, PA: Oncology Nursing Society; 1999: 32–41.
2. Recommendations for the Safe Handling of Parenteral Antineoplastic Drugs.
  Washington, DC: Division of Safety, Clinical Center Pharmacy Department and Cancer Nursing Services, National Institutes of Health; 1992 US Dept of Health and Human Services. Public Health Service Publication NIH 92–2621.
3. AMA Council on Scientific Affairs. Guidelines for Handling Parenteral Antineoplastics. JAMA 1985; 253(11):1590–1592.
4. National Study Commision on Cytotoxic Exposure – Recommendations for Handling of Cytotoxic Agents. 1987. Available from Louis P. Jeffrey, ScD., Chairman, National Study Commission on Cytotoxic Exposure, Massachusetts College of Pharmacy and Allied Health Sciences, 179 Longwood Avenue, Boston, MA 02115.
5. Clinical Oncology Society of Australia, Guidelines and Recommendations for Safe Handling of Antineoplastic Agents. Med J Australia 1983; 1:426–428.
6. Jones RB, Frank R, Mass T. Safe Handling of Chemotherapeutic Agents: A Report from the Mount Sinai Medical Center. CA-A Cancer J for Clin 1983; 33:258–263.
7. American Society of Hospital Pharmacists. ASHP Technical Assistance Bulletin on Handling Cytotoxic and Hazardous Drugs. AM J Hosp Pharm 1990; 47:1033–1049.
8. Controlling Occupational Exposure to Hazardous Drugs (OSHA Work-Practice Guidelines). Am J Health-Syst Pharm1996; 53:1669–1685.